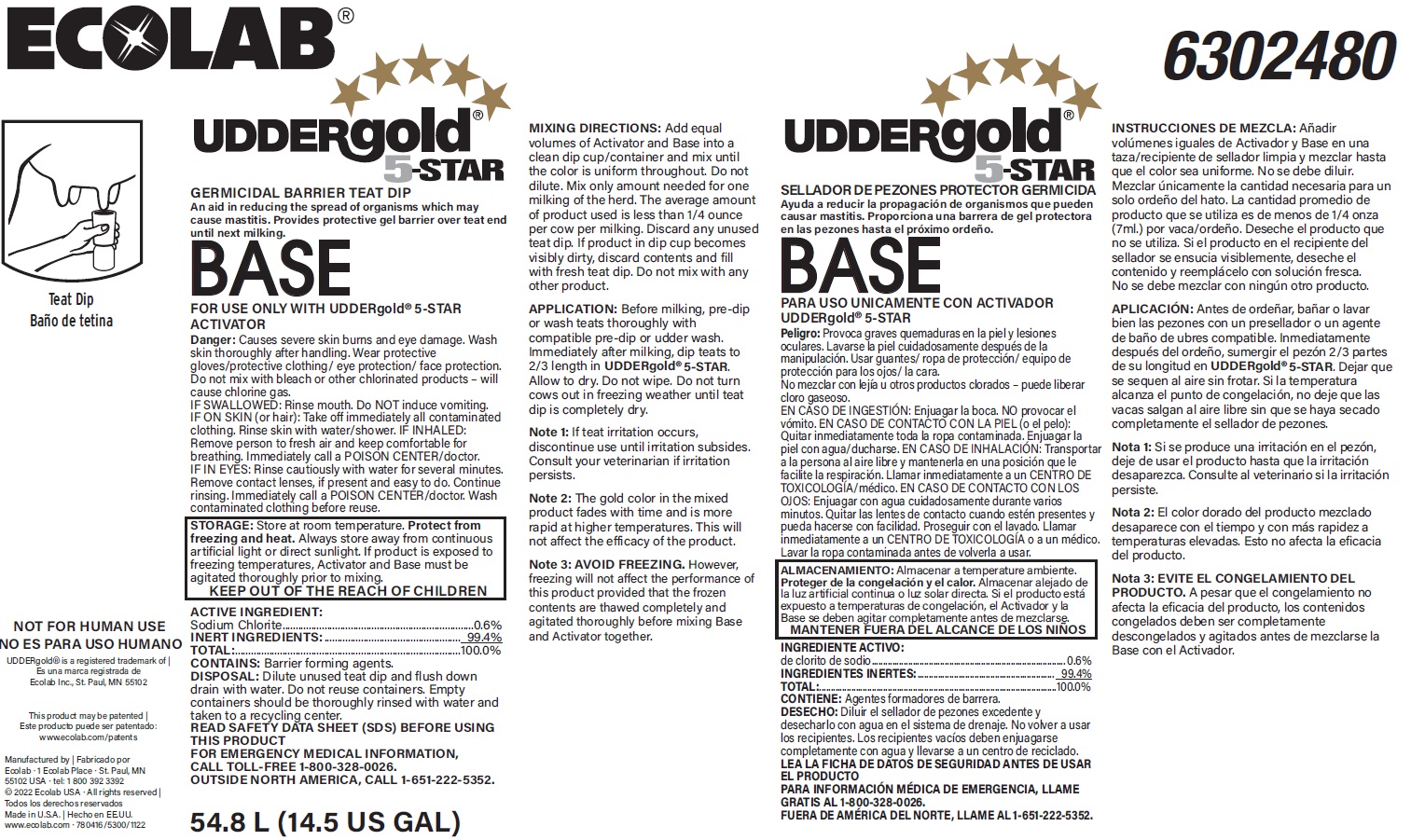 DRUG LABEL: Uddergold 5 Star Base
NDC: 47593-425 | Form: SOLUTION
Manufacturer: Ecolab Inc.
Category: animal | Type: OTC ANIMAL DRUG LABEL
Date: 20251029

ACTIVE INGREDIENTS: SODIUM CHLORITE 6 mg/1 mL
INACTIVE INGREDIENTS: WATER

SAFE HANDLING WARNING

NOT FOR HUMAN USE

KEEP OUT OF REACH OF CHILDREN

Danger: Causes severe skin burns and eye damage. Wash skin thoroughly after handling. Wear protective gloves/protective clothing/ eye protection/ face protection. Do not mix with bleach or other chlorinated products - will cause chlorine gas.

DISPOSAL: Dilute unused teat dip and flush down drain with water. Do not reuse containers. Empty containers should be thoroughly rinsed with water and taken to a recycling center.

STORAGE: Store at room temperature. Protect from freezing and heat. Always store away from continuous artificial light or direct sunlight. If product is exposed to freezing temperatures, Activator and Base must be agitated thoroughly prior to mixing.

VETERINARY INDICATIONS

Mixing Directions: Add equal volumes of Activator and Base into a clean dip cup/container and mix until the color is uniform throughout. Do not dilute. Mix only amount needed for one milking of the herd. The average amount of product used is less than 1/4 ounce per cow per milking. Discard any unused teat dip. If product in dip cup becomes visibly dirty, discard contents and fill with fresh teat dip. Do not mix with any other product.

APPLICATION: Before milking, pre-dip or wash teats thoroughly with compatible pre-dip or udder wash. Immediately after milking, dip teats to
2/3 length in UDDERgold®5-STAR. Allow to dry. Do not wipe. Do not turn cows out in freezing weather until teat dip is completely dry.

Note 1: If teat irritation occurs, discontinue use until irritation subsides. Consult your veterinarian if irritation persists.

Note 2: The gold color in the mixed product fades with time and is more rapid at higher temperatures. This will not affect the efficacy of the product.

Note 3: Avoid Freezing. However, freezing will not affect the performance of this product provided that the frozen contents are thawed completely and agitated thoroughly before mixing Base and Activator together.

OTHER SAFETY INFORMATION

IF SWALLOWED: Rinse mouth. Do NOT induce vomiting.

IF ON SKIN (or hair): Take off immediately all contaminated clothing. Rinse skin with water/shower.

IF INHALED: Remove person to fresh air and keep comfortable for breathing. Immediately call a POISON CENTER/doctor.

IF IN EYES: Rinse cautiously with water for several minutes. Remove contact lenses, if present and easy to do. Continue rinsing.

Immediately call a POISON CENTER/doctor. Wash contaminated clothing before reuse.

READ SAFETY DATA SHEET (SDS) BEFORE USING THIS PRODUCT

FOR EMERGENCY MEDICAL INFORMATION, CALL TOLL-FREE 1-800-328-0026.

OUTSIDE NORTH AMERICAN, CALL 1-651-222-5352

Representative Label and Principal Display Panel

ECOLAB

UDDERgold® 5-star

GERMICIDAL BARRIER TEAT DIP

An aid in reducing the spread of organisms which may cause mastitis.

Provides protective gel barrier over teat end until next milking.

BASE

FOR USE ONLY WITH UDDERgold 5-STAR ACTIVATOR

ACTIVE INGREDIENT:

Sodium Chlorite......................0.6%

INERT INGREDIENTS:.............99.4%

TOTAL:.................................100.0%

CONTAINS: Barrier forming agents.

Manufactured by

Ecolab - 1 Ecolab Place - St. Paul, MN

55102 USA - tel: 1 800 392 3392

54.8 L (14.5 US GAL)